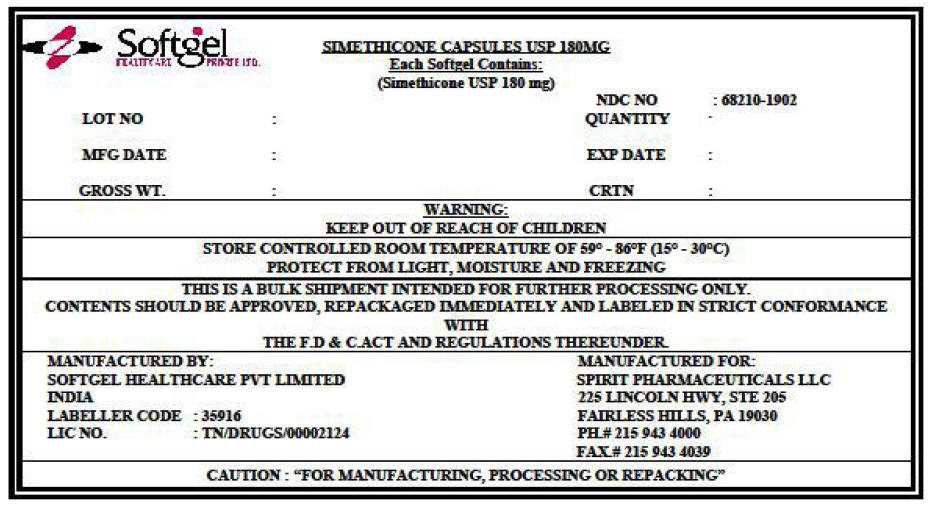 DRUG LABEL: SIMETHICONE
NDC: 68210-1902 | Form: CAPSULE, LIQUID FILLED
Manufacturer: SPIRIT PHARMACEUTICALS,LLC
Category: otc | Type: HUMAN OTC DRUG LABEL
Date: 20091202

ACTIVE INGREDIENTS: DIMETHICONE 180 mg/1 1
INACTIVE INGREDIENTS: GLYCERIN; GELATIN; TITANIUM DIOXIDE; SORBITOL; WATER; HYPROMELLOSE; FD&C YELLOW NO. 6; PEPPERMINT OIL

SIMETHICONE CAPSULES USP 180 MG

Drug Facts

Active ingredient (per softgel)

Simethicone 180 mg

Purpose

Antigas

Use

for the relief of

- pressure and bloating commonly referred to as gas

Warnings

Keep out of reach of children.

Directions

- adults: swallow with water 1 or 2 softgels as needed after meals and at bedtime
- do not exceed 2 softgels in 24 hours except under the advice and supervision of a physician

Other information

- store at a controlled room temperature 20-25°C (68-77°F)
- protect from heat and moisture

Inactive ingredients

FD&C yellow 6, gelatin, glycerin, hypromellose, peppermint oil, purified water, sorbitol, titanium dioxide

PRINCIPAL DISPLAY PANEL - Shipping Label

SIMETHICONE CAPSULES USP 180MG
Each Softgel Contains:
(Simethicone USP 180 mg)

LOT NO :

MFG DATE :

GROSS WT. :

NDC NO : 68210-1902
QUANTITY :

EXP DATE :

CRTN :

WARNING:
KEEP OUT OF REACH OF CHILDREN

STORE CONTROLLED ROOM TEMPERATURE OF 59° - 86°F (15° - 30°C)
PROTECT FROM LIGHT, MOISTURE AND FREEZING

THIS IS A BULK SHIPMENT INTENDED FOR FURTHER PROCESSING ONLY.
CONTENTS SHOULD BE APPROVED, REPACKAGED IMMEDIATELY AND LABELED IN STRICT CONFORMANCE
WITH
THE F.D & C.ACT AND REGULATIONS THEREUNDER.

MANUFACTURED BY:
SOFTGEL HEALTHCARE PVT LIMITED
INDIA
LABELLER CODE : 35916
LIC NO. : TN/DRUGS/00002124

MANUFACTURED FOR:
SPIRIT PHARMACEUTICALS LLC
225 LINCOLN HWY, STE 205
FAIRLESS HILLS, PA 19030
PH.# 215 943 4000
FAX.# 215 943 4039

CAUTION : "FOR MANUFACTURING, PROCESSING OR REPACKING"